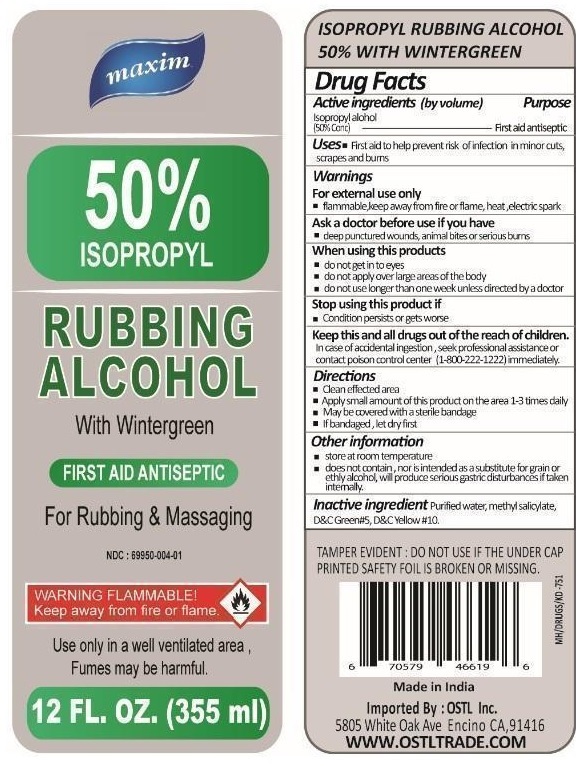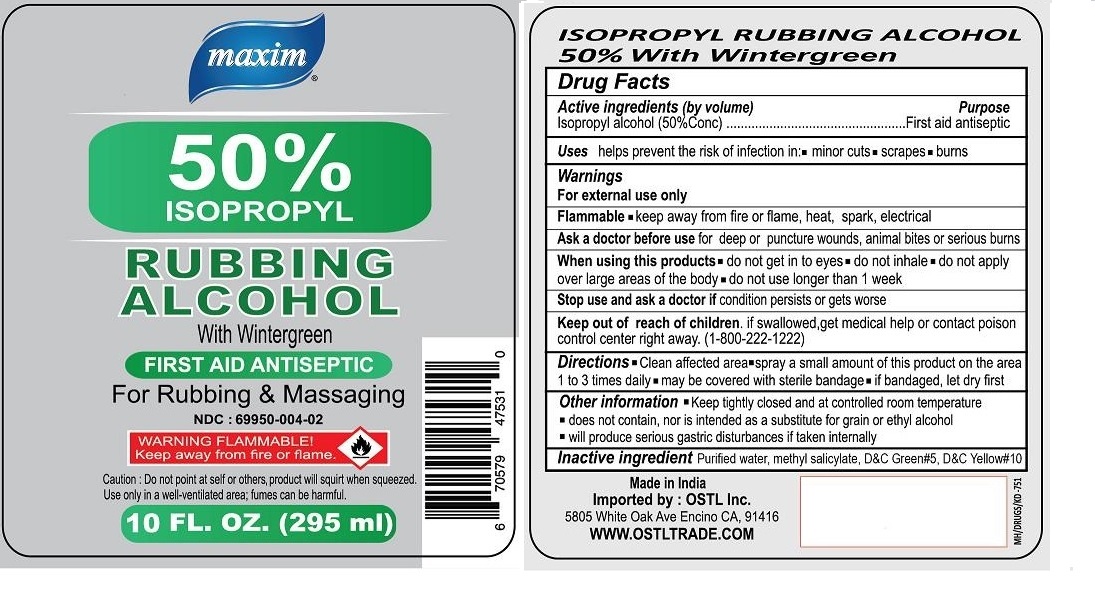 DRUG LABEL: maxim 50% ISOPROPYL RUBBING ALCOHOL With Wintergreen
NDC: 69950-004 | Form: LIQUID
Manufacturer: OSTL, INC.
Category: otc | Type: HUMAN OTC DRUG LABEL
Date: 20180727

ACTIVE INGREDIENTS: ISOPROPYL ALCOHOL 50 mL/100 mL
INACTIVE INGREDIENTS: WATER; METHYL SALICYLATE; D&C GREEN NO. 5; D&C YELLOW NO. 10

maxim 50% ISOPROPYL RUBBING ALCOHOL With Wintergreen

Active ingredients (by volume)

Isopropyl alcohol (50%Conc)

Purpose

First aid antiseptic

Uses

helps prevent the risk of infection in:• minor cuts • scrapes • burns

Warnings

For external use only

Flammable • keep away from fire or flame, heat, spark, electrical

Ask a doctor before use for deep or puncture wounds, animal bites or serious burns

When using this products • do not get in to eyes • do not inhale • do not apply over large areas of the body • do not use longer than 1 week

Stop use and ask a doctor if condition persists or gets worse

Keep out of reach of children. if swallowed, get medical help or contact poison control center right away. (1-800-222-1222)

Directions

• Clean affected area • spray a small amount of this product on the area 1 to 3 times daily • may be covered with sterile bandage • if bandaged, let dry first

Inactive ingredient

Purified water, methyl salicylate, D&C Green #5, D&C Yellow #10

Other information

• Keep tightly closed and at controlled room temperature • does not contain, nor is intended as a substitute for grain or ethyl alcohol • will produce serious gastric disturbances if taken internally

FIRST AID ANTISEPTIC

For Rubbing & Massaging

Caution: Do not point at self or others, product will squirt when squeezed. Use only in a well-ventilated area; fumes can be harmful.

Made in India

Imported by : OSTL Inc.

5805 White Oak Ave Encino CA, 91416

WWW.OSTLTRADE.COM

Packaging

355 mL

295 mL